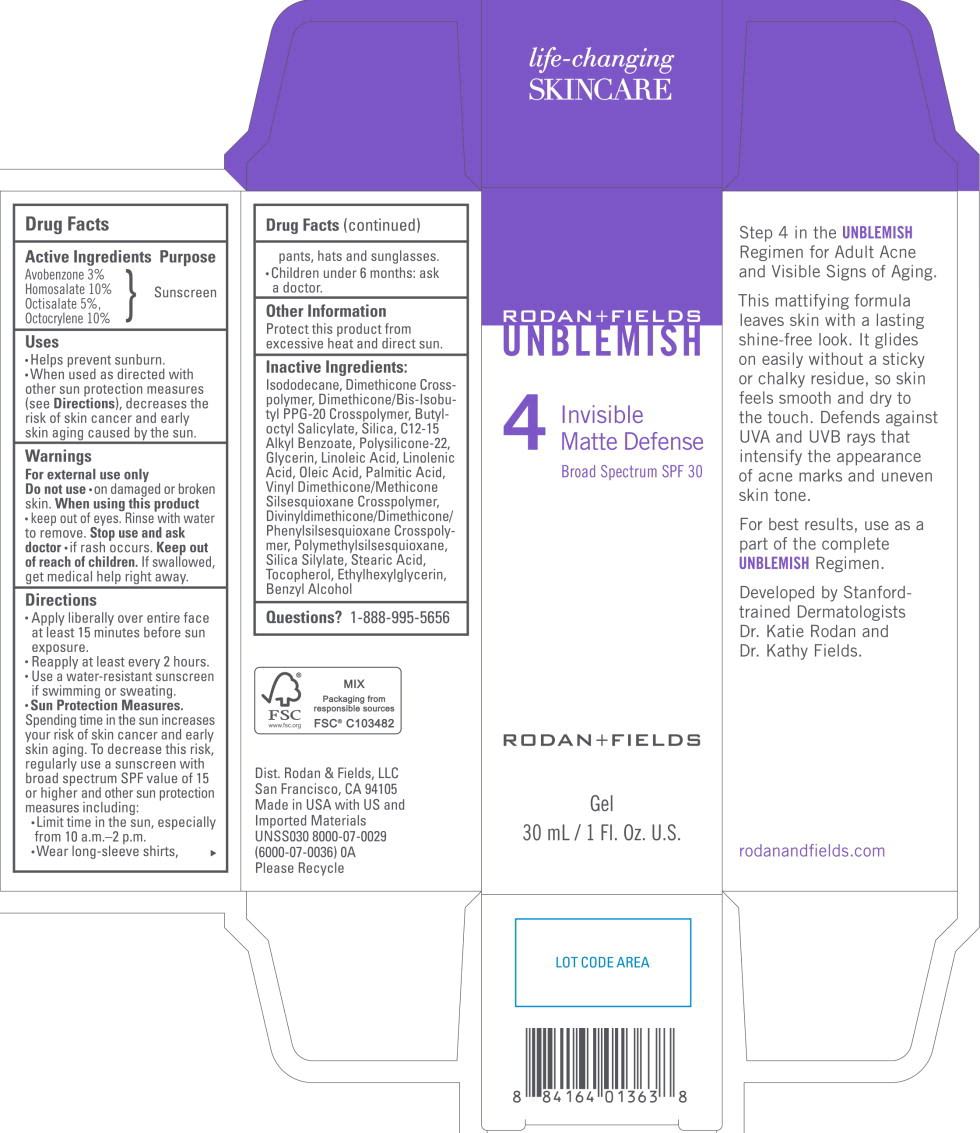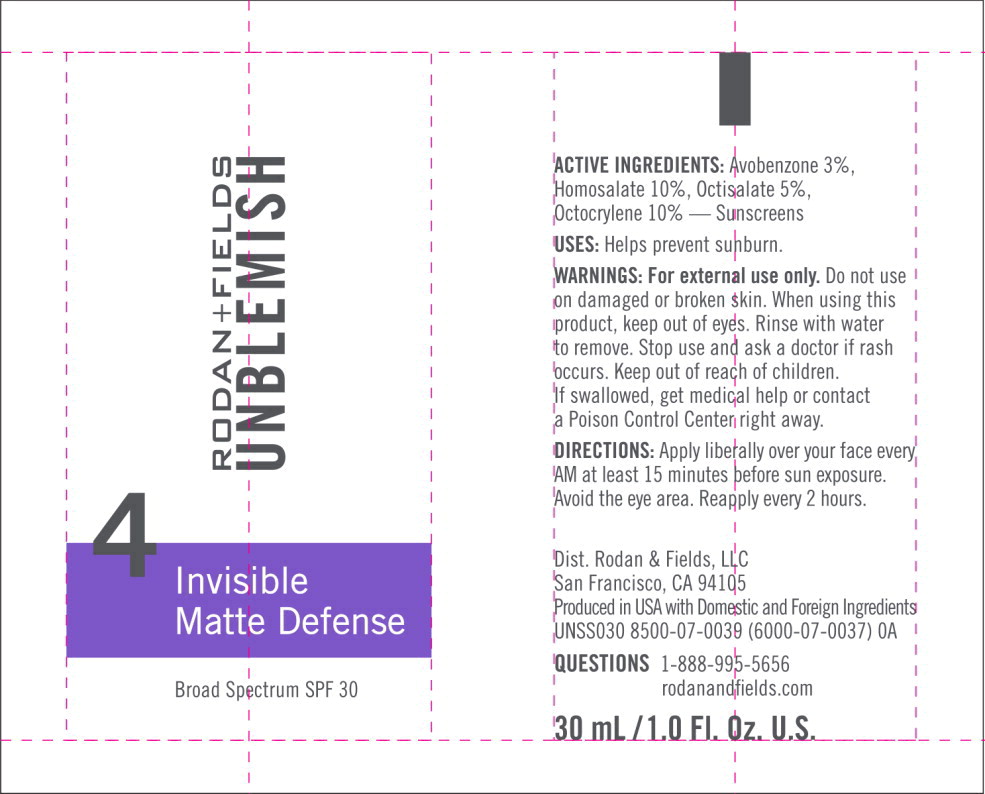 DRUG LABEL: UNBLEMISH Invisible Matte Defense
NDC: 14222-2131 | Form: GEL
Manufacturer: Rodan & Fields
Category: otc | Type: HUMAN OTC DRUG LABEL
Date: 20231127

ACTIVE INGREDIENTS: HOMOSALATE 0.1 g/1 mL; OCTOCRYLENE 0.1 g/1 mL; OCTISALATE 0.05 g/1 mL; AVOBENZONE 0.03 g/1 mL
INACTIVE INGREDIENTS: BENZYL ALCOHOL; BUTYLOCTYL SALICYLATE; ALKYL (C12-15) BENZOATE; DIMETHICONE/BIS-ISOBUTYL PPG-20 CROSSPOLYMER; ETHYLHEXYLGLYCERIN; GLYCERIN; ISODODECANE; LINOLEIC ACID; LINOLENIC ACID; OLEIC ACID; PALMITIC ACID; POLYMETHYLSILSESQUIOXANE (4.5 MICRONS); SILICON DIOXIDE; STEARIC ACID; TOCOPHEROL; VINYL DIMETHICONE/METHICONE SILSESQUIOXANE CROSSPOLYMER

Drug Facts

Active Ingredients

Avobenzone 3%

Homosalate 10%

Octisalate 5%,

Octocrylene 10%

Purpose

Sunscreen

Uses

- Helps prevent sunburn.
- When used as directed with other sun protection measures (see Directions), decreases the risk of skin cancer and early skin aging caused by the sun.

Warnings

For external use only

Do not use

- on damaged or broken skin.

When using this product

- keep out of eyes. Rinse with water to remove.

Stop use and ask doctor

- if rash occurs.

Keep out of reach of children. If swallowed, get medical help right away.

Directions

- Apply liberally over entire face at least 15 minutes before sun exposure.
- Reapply at least every 2 hours.
- Use a water-resistant sunscreen if swimming or sweating.
- Sun Protection Measures.
  Spending time in the sun increases your risk of skin cancer and early skin aging. To decrease this risk, regularly use a sunscreen with broad spectrum SPF value of 15 or higher and other sun protection measures including:
  - Limit time in the sun, especially from 10 a.m.-2 p.m.
  - Wear long-sleeve shirts, pants, hats and sunglasses.
  - Children under 6 months: ask a doctor.

Other Information

Protect this product from excessive heat and direct sun.

Inactive Ingredients:

lsododecane, Dimethicone Crosspolymer, Dimethicone/Bis-lsobutyl PPG-20 Crosspolymer, Butyloctyl Salicylate, Silica, C12-15 Alkyl Benzoate, Polysilicone-22, Glycerin, Linoleic Acid, Linolenic Acid, Oleic Acid, Palmitic Acid, Vinyl Dimethicone/Methicone Silsesquioxane Crosspolymer, Divinyldimethicone/Dimethicone/Phenylsilsesquioxane Crosspolymer, Polymethylsilsesquioxane, Silica Silylate, Stearic Acid, Tocopherol, Ethylhexylglycerin, Benzyl Alcohol

Questions?

1-888-995-5656

Principal Display Panel – 30 mL Carton Label

RODAN+FIELDS

UNBLEMISH

4
Invisible
Matte Defense

Broad Spectrum SPF 30

RODAN+FIELDS

Gel

30 mL/1 Fl. Oz. U.S.

Principal Display Panel – 30 mL Tube Label

RODAN+FIELDS

UNBLEMISH

4
Invisible
Matte Defense

Broad Spectrum SPF 30